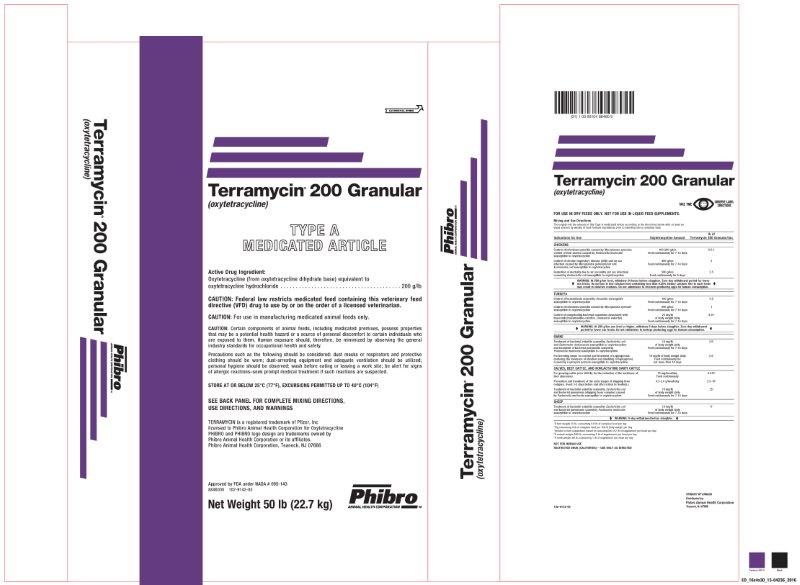 DRUG LABEL: Terramycin 200 Granular
NDC: 66104-9701 | Form: POWDER
Manufacturer: Phibro Animal Health
Category: animal | Type: VFD TYPE A MEDICATED ARTICLE ANIMAL DRUG LABEL
Date: 20231108

ACTIVE INGREDIENTS: OXYTETRACYCLINE HYDROCHLORIDE 200 g/0.45 kg
INACTIVE INGREDIENTS: CALCIUM CARBONATE; RICE BRAN; MINERAL OIL

Terramycin® 200 Granular
(oxytetracycline)
TYPE A MEDICATED ARTICLE

Active Drug Ingredient:

Oxytetracycline (from oxytetracycline dihydrate base) equivalent to

oxytetracycline hydrochloride . . . . . . . . . . . . . . . . . . . . . . . . . . . . . . . . . . . . . . . 200 g/lb

CAUTION:

CAUTION: Federal law restricts medicated feed containing this veterinary feed directive (VFD) drug to use by or on the order of a licensed veterinarian.

CAUTION: For use in manufacturing medicated animal feeds only.

CAUTION: Certain components of animal feeds, including medicated premixes, possess properties that may be a potential health hazard or a source of personal discomfort to certain individuals who are exposed to them. Human exposure should, therefore, be minimized by observing the general industry standards for occupational health and safety.

Precautions such as the following should be considered: dust masks or respirators and protective clothing should be worn; dust-arresting equipment and adequate ventilation should be utilized; personal hygiene should be observed; wash before eating or leaving a work site; be alert for signs of allergic reactions–seek prompt medical treatment if such reactions are suspected.

FOR USE IN DRY FEEDS ONLY. NOT FOR USE IN LIQUID FEED SUPPLEMENTS.

Mixing and Use Directions

Thoroughly mix the amount of this Type A medicated article according to the directions below with at least an equal amount by weight of feed formula ingredients prior to blending into a complete feed.

Indications for Use | Oxytetracycline; Amount | lb of; Terramycin 200 Granular /ton
CHICKENS
Control of infectious synovitis caused by Mycoplasma synoviae; control of fowl cholera caused by Pasteurella multocida susceptible to oxytetracycline | 100-200 g/ton; Feed continuously for 7-14 days | 0.5-1
Control of chronic respiratory disease (CRD) and air sac infection caused by Mycoplasma gallisepticum and Escherichia coli susceptible to oxytetracycline | 400 g/ton; Feed continuously for 7-14 days | 2
Reduction of mortality due to air sacculitis (air sac infection) caused by Escherichia coli susceptible to oxytetracycline | 500 g/ton; Feed continuously for 5 days | 2.5
WARNING: At 500 g/ton level, withdraw 24 hours before slaughter. Zero-day withdrawal period for lower use levels. Do not use in low-calcium feed containing less than 0.55 dietary calcium. Use in such may result in violative residues. Do not administer to chickens producing eggs for human consumption.

TURKEYS
Control of hexamitiasis caused by Hexamita meleagridis susceptible to oxytetracycline | 100 g/ton; Feed continuously for 7-14 days | 0.5
Control of infectious synovitis caused by Mycoplasma synoviae susceptible to oxytetracycline | 200 g/ton; Feed continuously for 7-14 days | 1
Control of complicating bacterial organisms associated with bluecomb (transmissible enteritis, coronaviral enteritis) susceptible to oxytetracycline | 25 mg/lb; of body weight daily; Feed continuously for 7-14 days | 4.15^1
WARNING: At 200 g/ton use level or higher, withdraw 5 days before slaughter. Zero-day withdrawal period for lower use levels. Do not administer to turkeys producing eggs for human consumption.
SWINE
Treatment of bacterial enteritis caused by Escherichia coli and Salmonella choleraesuis susceptible to oxytetracycline and treatment of bacterial pneumonia caused by Pasteurella multocida susceptible to oxytetracycline | 10 mg/lb; of body weight daily; Feed continuously for 7-14 days | 2.5^2
For breeding swine for control and treatment of Leptospirosis (reducing the incidence of abortion and shedding of leptospirae) caused by Leptospira pomona susceptible to oxytetracycline | 10 mg/lb of body weight daily; Feed continuously for; not more than 14 days | 2.5^2
CALVES, BEEF CATTLE, AND NONLACTATING DAIRY CATTLE
For growing cattle (over 400 lb) for reduction of liver condemnation due to liver abscesses | 75 mg/head/day; Feed continuously | 0.375^3
Prevention and treatment of the early stages of shipping fever complex. (Feed 3-5 days before and after arrival in feedlots.) | 0.5-2.0 g/head/day | 2.5-10^3
Treatment of bacterial enteritis caused by Escherichia coli and bacterial pneumonia (shipping fever complex) caused by Pasteurella multocida susceptible to oxytetracycline | 10 mg/lb; of body weight daily; Feed continuously for 7-14 days | 25^4
SHEEP
Treatment of bacterial enteritis caused by Escherichia coli and bacterial pneumonia caused by Pasteurella multocida susceptible to oxytetracycline | 10 mg/lb; of body weight daily; Feed continuously for 7-14 days | 6^5
WARNING: 5-day withdrawal before slaughter.
^1If bird weighs 10 lb, consuming 0.6 lb of complete feed per day
^2Pig consuming 4 lb of complete feed per 100 lb body weight per day
^3Include in feed supplement based on consumption of 2 lb of supplement per head per day
^4If animal weighs 500 lb, consuming 2 lb of supplement per head per day
^5If lamb weighs 60 lb, consuming 1 lb of supplement per head per day

NOT FOR HUMAN USE

RESTRICTED DRUG (CALIFORNIA) – USE ONLY AS DIRECTED

SEE BACK PANEL FOR COMPLETE MIXING DIRECTIONS,

USE DIRECTIONS, AND WARNINGS

Terramycin is a registered trademark of Pfizer, Inc.,

licensed to Phibro Animal Health, for Oxytetracycline

PHIBRO and PHIBRO logo design are trademarks owned by

Phibro Animal Health Corporation or its affiliates

Phibro Animal Health Corporation, Teaneck, NJ 07666

Net Weight 50 lb (22.7 kg)

Approved by FDA under NADA # 095-143

8846000

102-9142-020-05

Terramycin 200 Granular